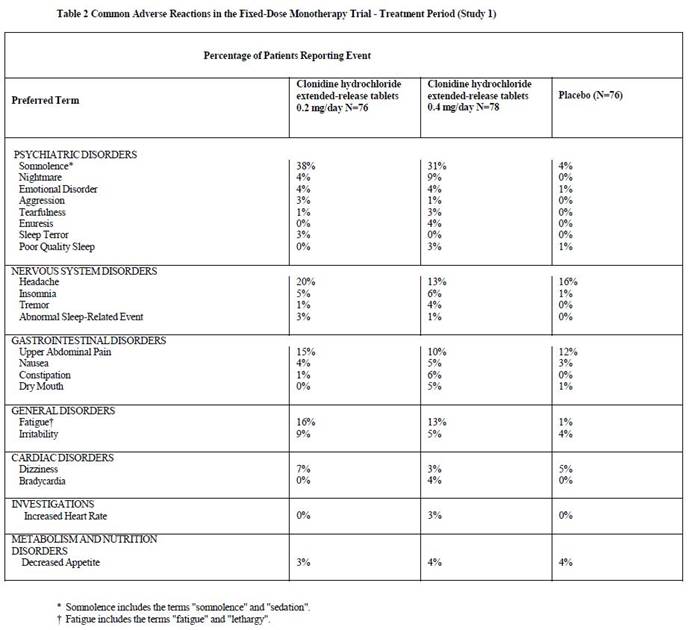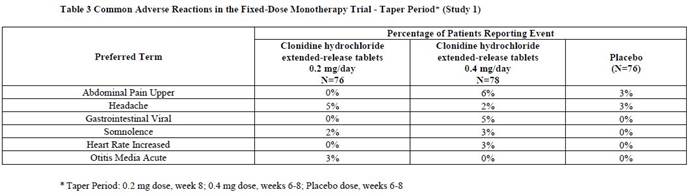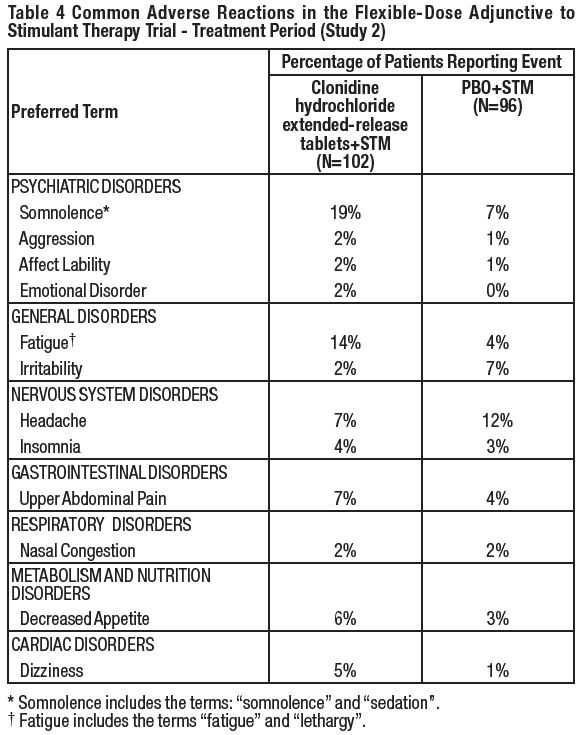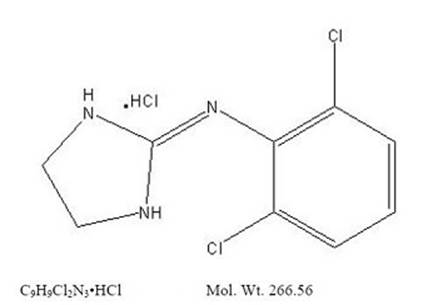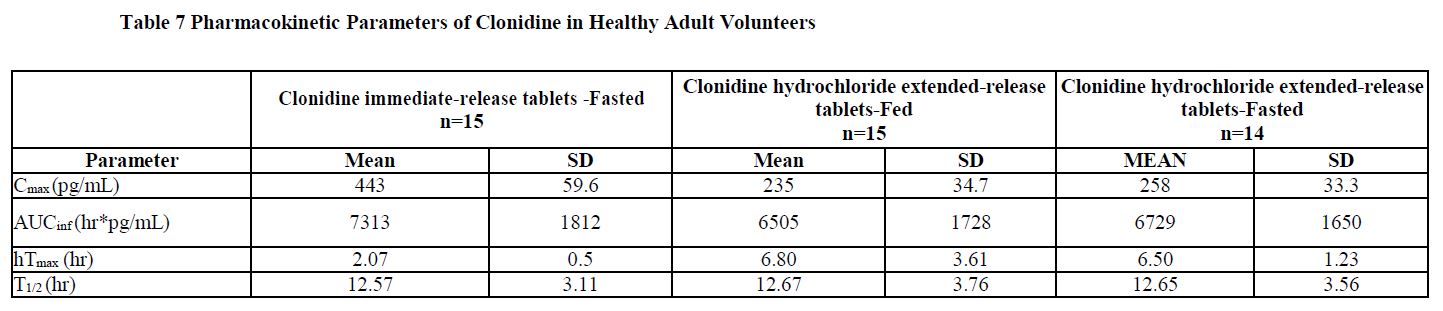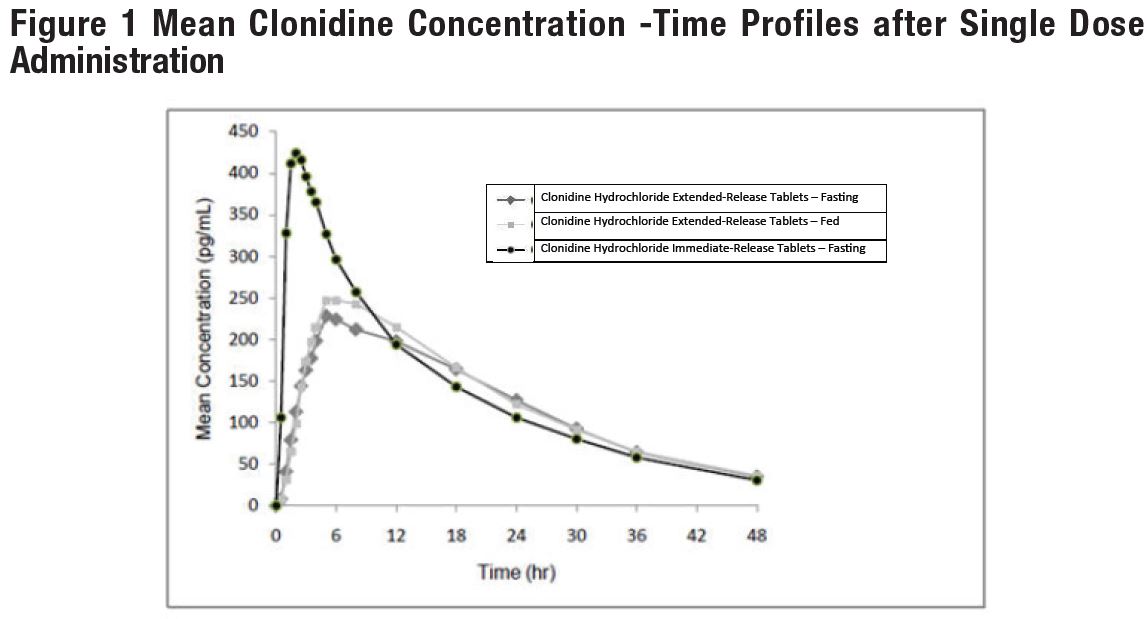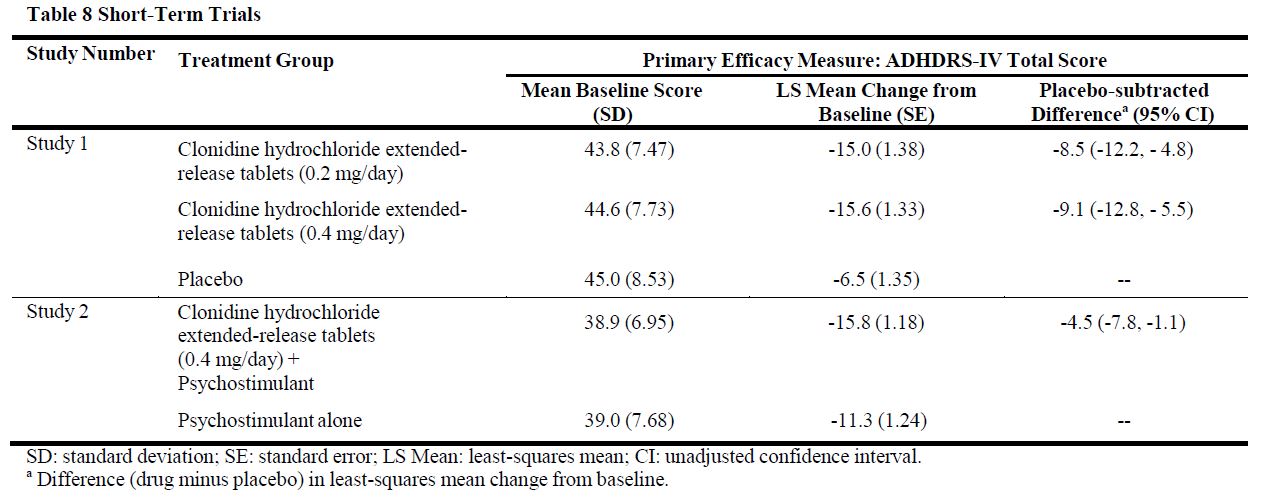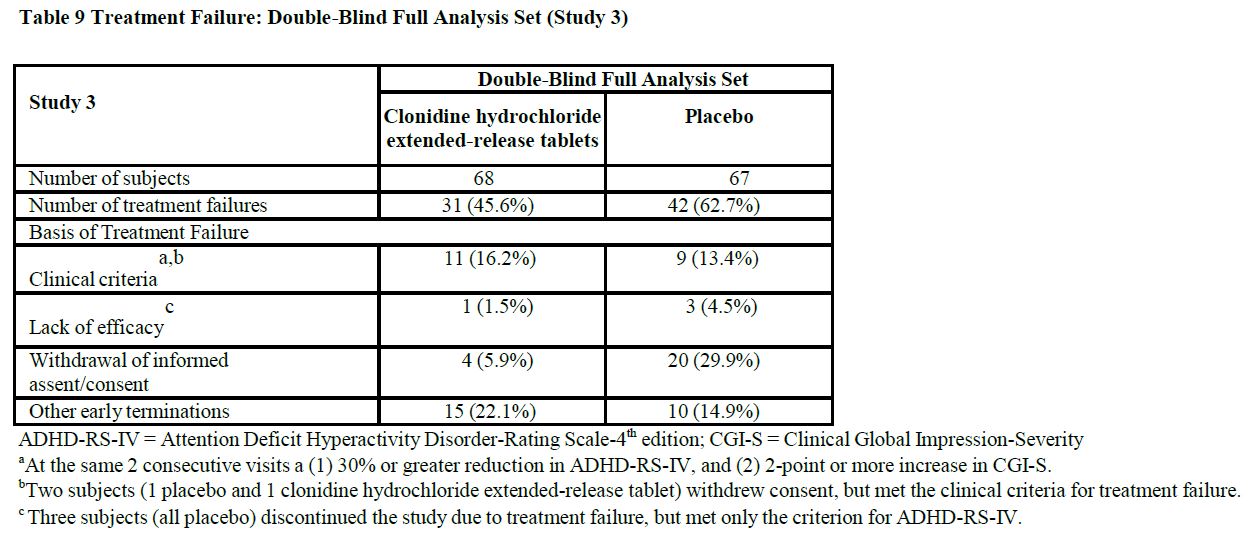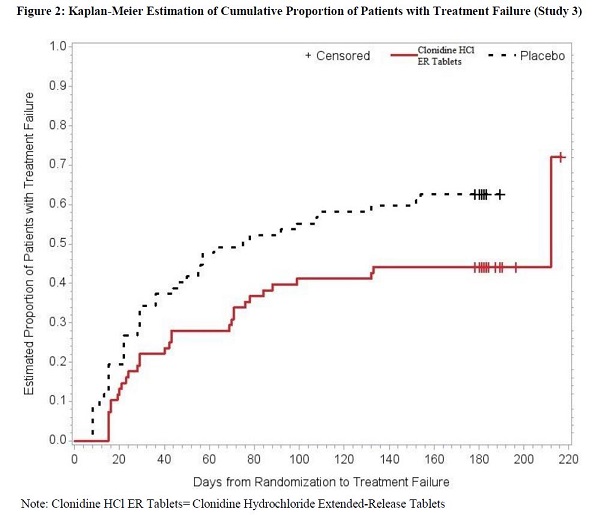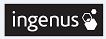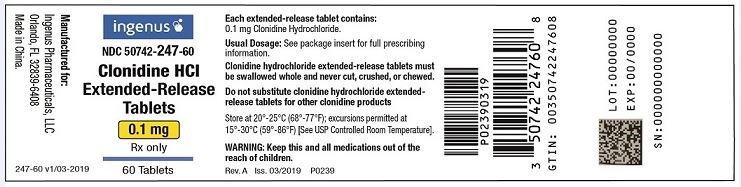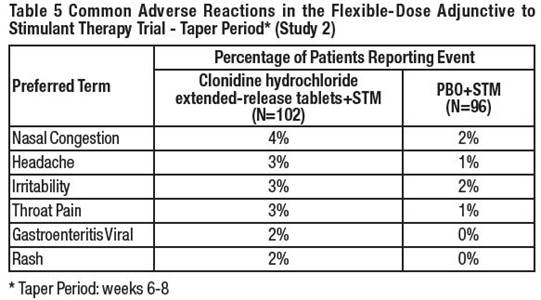 DRUG LABEL: Clonidine
NDC: 50742-247 | Form: TABLET, EXTENDED RELEASE
Manufacturer: Ingenus Pharmaceuticals, LLC
Category: prescription | Type: HUMAN PRESCRIPTION DRUG LABEL
Date: 20251205

ACTIVE INGREDIENTS: CLONIDINE HYDROCHLORIDE 0.1 mg/1 1
INACTIVE INGREDIENTS: POVIDONE; SODIUM LAURYL SULFATE; LACTOSE MONOHYDRATE; CELLULOSE, MICROCRYSTALLINE; HYPROMELLOSE 2208 (15000 MPA.S); SILICON DIOXIDE; MAGNESIUM STEARATE

HIGHLIGHTS OF PRESCRIBING INFORMATION

These highlights do not include all the information needed to use CLONIDINE HYDROCHLORIDE EXTENDED-RELEASE TABLETS safely and effectively.
See full prescribing information for CLONIDINE HYDROCHLORIDE EXTENDED-RELEASE TABLETS.
CLONIDINE HYDROCHLORIDE extended-release tablets, for oral use
Initial U.S. Approval: 1974

1 INDICATIONS AND USAGE

Clonidine hydrochloride extended-release tablets is a centrally acting alpha2-adrenergic agonist indicated for the treatment of attention deficit hyperactivity disorder (ADHD) as monotherapy or as adjunctive therapy to stimulant medications. (1)

2 DOSAGE AND ADMINISTRATION

• Start with one 0.1 mg tablet at bedtime for one week. Increase daily dosage in increments of 0.1 mg/day at weekly intervals until the desired response is achieved. Take twice a day, with either an equal or higher split dosage being given at bedtime, as depicted below (2.2)

Total Daily Dose | M orning Dose | Bedtime Dose
0.1 mg/day |  | 0.1 mg
0.2 mg/day | 0.1 mg | 0.1 mg
0.3 mg/day | 0.1 mg | 0.2 mg
0.4 mg/day | 0.2 mg | 0.2 mg

- Do not crush, chew or break tablet before swallowing. (2.1)
- Do not substitute for other clonidine products on a mg-per-mg basis, because of differing pharmacokinetic profiles. (2.1)
- When discontinuing, taper the dose in decrements of no more than 0.1 mg every 3 to 7 days to avoid rebound hypertension. (2.3)

3 DOSAGE FORMS AND STRENGTHS

Extended-release tablets: 0.1 mg, not scored. (3)

4 CONTRAINDICATIONS

History of a hypersensitivity reaction to clonidine. Reactions have included generalized rash, urticaria, angioedema.(4)

5 WARNINGS AND PRECAUTIONS

• Hypotension/bradycardia/syncope: Titrate slowly and monitor vital signs frequently in patients at risk for hypotension, heart block, bradycardia, syncope, cardiovascular disease, vascular disease, cerebrovascular disease or chronic renal failure. Measure heart rate and blood pressure prior to initiation of therapy, following dose increases, and periodically while on therapy. Avoid concomitant use of drugs with additive effects unless clinically indicated. Advise patients to avoid becoming dehydrated or overheated. (5.1)

• Somnolence/Sedation: Has been observed with clonidine hydrochloride extended-release tablets. Consider the potential for additive sedative effects with CNS depressant drugs. Caution patients against operating heavy equipment or driving until they know how they respond to clonidine hydrochloride extended-release tablets. (5.2)

• Cardiac Conduction Abnormalities: May worsen sinus node dysfunction and atrioventricular (AV) block, especially in patients taking other sympatholytic drugs. Titrate slowly and monitor vital signs frequently. (5.5)

6 ADVERSE REACTIONS

Most common adverse reactions (incidence at least 5% and twice the rate of placebo) as monotherapy in ADHD: somnolence, fatigue, irritability, nightmare, insomnia, constipation, dry mouth. (6.1)

Most common adverse reactions (incidence at least 5% and twice the rate of placebo) as adjunct therapy to psychostimulant in ADHD: somnolence, fatigue, decreased appetite, dizziness. (6.1)

To report SUSPECTED ADVERSE REACTIONS, contact Ingenus Pharmaceuticals, LLC Toll-Free at 1-877-748-1970 or FDA at 1-800-FDA-1088 or www.fda.gov/medwatch.

7 DRUG INTERACTIONS

• Sedating Drugs: Clonidine may potentiate the CNS-depressive effects of alcohol, barbiturates or other sedating drugs. (7)

• Tricyclic Antidepressants: May reduce the hypotensive effect of clonidine. (7)

• Drugs Known to Affect Sinus Node Function or AV Nodal Conduction: Caution is warranted in patients receiving clonidine concomitantly with agents known to affect sinus node function or AV nodal conduction (e.g., digitalis, calcium channel blockers and beta-blockers) due to a potential for additive effects such as bradycardia and AV block. (7)

• Antihypertensive drugs: Use caution when coadministered with clonidine hydrochloride extended-release tablets. (7)

8 USE IN SPECIFIC POPULATIONS

• Renal Impairment: The dosage of clonidine hydrochloride extended-release tablets must be adjusted according to the degree of impairment, and patients should be carefully monitored. (8.6, 12.3)

FULL PRESCRIBING INFORMATION

1 INDICATIONS AND USAGE

Clonidine hydrochloride extended-release tablets are indicated for the treatment of attention deficit hyperactivity disorder (ADHD) as monotherapy and as adjunctive therapy to stimulant medications [see Clinical Studies (14)].

2 DOSAGE AND ADMINISTRATION

2.1 General Dosing Information

Clonidine hydrochloride extended-release tablets is an extended-release tablet to be taken orally with or without food. Swallow tablets whole. Do not crush, chew, or break tablets because this will increase the rate of clonidine release.

Due to the lack of controlled clinical trial data and differing pharmacokinetic profiles, substitution of clonidine hydrochloride extended-release tablets for other clonidine products on a mg-per-mg basis is not recommended [see Clinical Pharmacology (12.3)].

2.2 Dose Selection

The dose of clonidine hydrochloride extended-release tablets, administered either as monotherapy or as adjunctive therapy to a psychostimulant, should be individualized according to the therapeutic needs and response of the patient. Dosing should be initiated with one 0.1 mg tablet at bedtime, and the daily dosage should be adjusted in increments of 0.1 mg/day at weekly intervals until the desired response is achieved. Doses should be taken twice a day, with either an equal or higher split dosage being given at bedtime (see Table 1).

Table 1 Clonidine hydrochloride extended-release tablets Dosing Guidance

Total Daily Dose | Morning Dose | Bedtime Dose
0.1 mg/day |  | 0.1 mg
0.2 mg/day | 0.1 mg | 0.1 mg
0.3 mg/day | 0.1 mg | 0.2 mg
0.4 mg/day | 0.2 mg | 0.2 mg

Doses of clonidine hydrochloride extended-release tablets higher than 0.4 mg/day (0.2 mg twice daily) were not evaluated in clinical trials for ADHD and are not recommended.

When clonidine hydrochloride extended-release tablets is being added-on to a psychostimulant, the dose of the psychostimulant can be adjusted depending on the patient's response to clonidine hydrochloride extended-release tablets.

2.3 Discontinuation

When discontinuing clonidine hydrochloride extended-release tablets, the total daily dose should be tapered in decrements of no more than 0.1 mg every 3 to 7 days to avoid rebound hypertension [see Warnings and Precautions (5.3)].

2.4 Missed Doses

If patients miss a dose of clonidine hydrochloride extended-release tablets, they should skip that dose and take the next dose as scheduled. Do not take more than the prescribed total daily amount of clonidine hydrochloride extended-release tablets in any 24-hour period.

3 DOSAGE FORMS AND STRENGTHS

Clonidine hydrochloride extended-release tablets are available as 0.1 mg strength extended-release tablets. The 0.1 mg tablets are white or off white, non-scored, round biconvex with debossing on one side. Clonidine hydrochloride extended-release tablets must be swallowed whole and never crushed, cut or chewed.

4 CONTRAINDICATIONS

Clonidine hydrochloride extended-release tablets are contraindicated in patients with a history of a hypersensitivity reaction to clonidine. Reactions have included generalized rash, urticaria, and angioedema [see Adverse Reactions (6)].

5 WARNINGS AND PRECAUTIONS

5.1 Hypotension/Bradycardia

Treatment with clonidine hydrochloride extended-release tablets can cause dose-related decreases in blood pressure and heart rate [see Adverse Reactions (6.1)]. Measure heart rate and blood pressure prior to initiation of therapy, following dose increases, and periodically while on therapy. Titrate clonidine hydrochloride extended-release tablets slowly in patients with a history of hypotension, and those with underlying conditions that may be worsened by hypotension and bradycardia; e.g., heart block, bradycardia, cardiovascular disease, vascular disease, cerebrovascular disease, or chronic renal failure. In patients who have a history of syncope or may have a condition that predisposes them to syncope, such as hypotension, orthostatic hypotension, bradycardia, or dehydration, advise patients to avoid becoming dehydrated or overheated. Monitor blood pressure and heart rate, and adjust dosages accordingly in patients treated concomitantly with antihypertensives or other drugs that can reduce blood pressure or heart rate or increase the risk of syncope.

5.2 Sedation and Somnolence

Somnolence and sedation were commonly reported adverse reactions in clinical studies. In patients that completed 5 weeks of therapy in a controlled, fixed dose pediatric monotherapy study, 31% of patients treated with 0.4 mg/day and 38% treated with 0.2 mg/day versus 4% of placebo treated patients reported somnolence as an adverse event. In patients that completed 5 weeks of therapy in a controlled flexible dose pediatric adjunctive to stimulants study, 19% of patients treated with clonidine hydrochloride extended-release tablets +stimulant versus 7% treated with placebo+stimulant reported somnolence. Before using clonidine hydrochloride extended-release tablets with other centrally active depressants (such as phenothiazines, barbiturates, or benzodiazepines), consider the potential for additive sedative effects. Caution patients against operating heavy equipment or driving until they know how they respond to treatment with clonidine hydrochloride extended-release tablets. Advise patients to avoid use with alcohol.

5.3 Rebound Hypertension

Abrupt discontinuation of clonidine hydrochloride extended-release tablets can cause rebound hypertension. In adults with hypertension, sudden cessation of clonidine hydrochloride extended- release formulation treatment in the 0.2 to 0.6 mg/day range resulted in reports of headache, tachycardia, nausea, flushing, warm feeling, brief lightheadedness, tightness in chest, and anxiety. In adults with hypertension, sudden cessation of treatment with immediate-release clonidine has, in some cases, resulted in symptoms such as nervousness, agitation, headache, and tremor accompanied or followed by a rapid rise in blood pressure and elevated catecholamine concentrations in the plasma.

No studies evaluating abrupt discontinuation of clonidine hydrochloride extended-release tablets in children with ADHD have been conducted; however, to minimize the risk of rebound hypertension, gradually reduce the dose of clonidine hydrochloride extended-release tablets in decrements of no more than 0.1 mg every 3 to 7 days. Patients should be instructed not to discontinue clonidine hydrochloride extended-release tablets therapy without consulting their physician due to the potential risk of withdrawal effects.

5.4 Allergic Reactions

In patients who have developed localized contact sensitization to clonidine transdermal system, continuation of clonidine transdermal system or substitution of oral clonidine hydrochloride extended-release tablets therapy may be associated with the development of a generalized skin rash.

In patients who develop an allergic reaction from clonidine transdermal system, substitution of oral clonidine hydrochloride extended-release tablets may also elicit an allergic reaction (including generalized rash, urticaria, or angioedema).

5.5 Cardiac Conduction Abnormalities

The sympatholytic action of clonidine may worsen sinus node dysfunction and atrioventricular (AV) block, especially in patients taking other sympatholytic drugs. There have been post-marketing reports of patients with conduction abnormalities and/or taking other sympatholytic drugs who developed severe bradycardia requiring IV atropine, IV isoproterenol, and temporary cardiac pacing while taking clonidine. Titrate clonidine hydrochloride extended-release tablets slowly and monitor vital signs frequently in patients with cardiac conduction abnormalities or patients concomitantly treated with other sympatholytic drugs.

6 ADVERSE REACTIONS

The following serious adverse reactions are described in greater detail elsewhere in labeling:

- Hypotension/bradycardia [see Warnings and Precautions (5.1)]
- Sedation and somnolence [see Warnings and Precautions (5.2)]
- Rebound hypertension [see Warnings and Precautions (5.3)]
- Allergic reactions [see Warnings and Precautions (5.4)]
- Cardiac Conduction Abnormalities [see Warnings and Precautions (5.5)]

6.1 Clinical Trial Experience

Because clinical trials are conducted under widely varying conditions, adverse reaction rates observed in the clinical trials of a drug cannot be directly compared to rates in the clinical trials of another drug and may not reflect the rates observed in practice.

Two clonidine hydrochloride extended-release tablets ADHD clinical studies (Study 1, CLON-301 and Study 2, CLON-302) evaluated 256 patients in two 8-week placebo-controlled studies.

A third clonidine hydrochloride extended-release tablets ADHD clinical study (Study 3, SHN-KAP-401) evaluated 135 children and adolescents in a 40- week placebo-controlled randomized-withdrawal study.

Study 1: Fixed-dose clonidine hydrochloride extended-release tablets Monotherapy

Study 1 (CLON-301) was a short-term, multi-center, randomized, double-blind, placebo-controlled study of two fixed doses (0.2 mg/day or 0.4 mg/day) of clonidine hydrochloride extended-release tablets in children and adolescents (6 to 17 years of age) who met DSM-IV criteria for ADHD hyperactive or combined inattentive/hyperactive subtypes.

Most Common Adverse Reactions (incidence of >=5% and at least twice the rate of placebo): somnolence, fatigue, irritability, insomnia, nightmare, constipation, dry mouth.

Adverse Events Leading to Discontinuation of clonidine hydrochloride extended-release tablets –Five patients (7%) in the low dose group (0.2 mg), 15 patients (20%) in the high dose group (0.4 mg), and 1 patient in the placebo group (1%) reported adverse reactions that led to discontinuation. The most common adverse reactions that led to discontinuation were somnolence and fatigue.

Commonly observed adverse reactions (incidence of >=2% in either active treatment group and greater than the rate on placebo) during the treatment period are listed in Table 2.

Commonly observed adverse reactions (incidence of >=2% in either active treatment group and greater than the rate on placebo) during the taper period are listed in Table 3.

Study 2: Flexible-dose clonidine hydrochloride extended-release tablets as Adjunctive Therapy to Psychostimulants

Study 2 (CLON-302) was a short-term, randomized, double-blind, placebo-controlled study of a flexible dose of clonidine hydrochloride extended-release tablets as adjunctive therapy to a psychostimulant in children and adolescents (6 to 17 years) who met DSM-IV criteria for ADHD hyperactive or combined inattentive/hyperactive subtypes, during which clonidine hydrochloride extended-release tablets were initiated at 0.1 mg/day and titrated up to 0.4 mg/day over a 3-week period. Most clonidine hydrochloride extended-release tablets treated patients (75.5%) were escalated to the maximum dose of 0.4 mg/day.

Most Common Adverse Reactions (incidence of >=5% and at least twice the rate of placebo): somnolence, fatigue, decreased appetite, dizziness.

Adverse Events Leading to Discontinuation – There was one patient in the CLON+STM group (1%) who discontinued because of an adverse event (severe bradyphrenia, with severe fatigue).

Commonly observed adverse reactions (incidence of >=2% in the treatment group and greater than the rate on placebo) during the treatment period are listed in Table 4.

Commonly observed adverse reactions (incidence of >=2% in the treatment group and greater than the rate on placebo) during the taper period are listed in Table 5.

Adverse Reactions Leading to Discontinuation

Thirteen percent (13%) of patients receiving clonidine hydrochloride extended-release tablets discontinued from the pediatric monotherapy study due to adverse events, compared to 1% in the placebo group. The most common adverse reactions leading to discontinuation of clonidine hydrochloride extended-release tablets monotherapy treated patients were from somnolence/sedation (5%) and fatigue (4%).

Effect on Blood Pressure and Heart Rate

In patients that completed 5 weeks of treatment in a controlled, fixed-dose monotherapy study in pediatric patients, during the treatment period the maximum placebo-subtracted mean change in systolic blood pressure was -4.0 mmHg on clonidine hydrochloride extended-release tablets 0.2 mg/day and -8.8 mmHg on clonidine hydrochloride extended-release tablets 0.4 mg/day. The maximum placebo-subtracted mean change in diastolic blood pressure was -4.0 mmHg on clonidine hydrochloride extended-release tablets 0.2 mg/day and -7.3 mmHg on clonidine hydrochloride extended-release tablets 0.4 mg/day. The maximum placebo-subtracted mean change in heart rate was -4.0 beats per minute on clonidine hydrochloride extended-release tablets 0.2 mg/day and -7.7 beats per minute on clonidine hydrochloride extended-release tablets 0.4 mg/day.

During the taper period of the fixed-dose monotherapy study the maximum placebo-subtracted mean change in systolic blood pressure was +3.4 mmHg on clonidine hydrochloride extended-release tablets 0.2 mg/day and -5.6 mmHg on clonidine hydrochloride extended-release tablets 0.4 mg/day. The maximum placebo-subtracted mean change in diastolic blood pressure was +3.3 mmHg on clonidine hydrochloride extended-release tablets 0.2 mg/day and -5.4 mmHg on clonidine hydrochloride extended-release tablets 0.4 mg/day. The maximum placebo-subtracted mean change in heart rate was -0.6 beats per minute on clonidine hydrochloride extended-release tablets 0.2 mg/day and -3.0 beats per minute on clonidine hydrochloride extended-release tablets 0.4 mg/day.

6.2 Postmarketing Experience

The following adverse reactions have been identified during post-approval use of clonidine hydrochloride extended-release tablets. Because these reactions are reported voluntarily from a population of uncertain size, it is not always possible to reliably estimate their frequency or establish a causal relationship to drug exposure.

These events exclude those already mentioned in 6.1:

Psychiatric: hallucinations

Cardiovascular: Q-T prolongation

7 DRUG INTERACTIONS

The following have been reported with other oral immediate release formulations of clonidine:

Table 6 Clinically Important Drug Interactions

Concomitant Drug Name or Drug Class | Clinical Rationale | Clinical Recommendation
Tricyclic antidepressants | Increase blood pressure and may counteract clonidine's hypotensive effects | Monitor blood pressure and adjust as needed
Antihypertensive drugs | Potentiate clonidine's hypotensive effects | Monitor blood pressure and adjust as needed
CNS depressants | Potentiate sedating effects | Avoid use
Drugs that affect sinus node function or AV node conduction (e.g., digitalis, calcium channel blockers, beta blockers) | Potentiate bradycardia and risk of AV block | Avoid use

8 USE IN SPECIFIC POPULATIONS

8.1 Pregnancy

Pregnancy Exposure Registry

There is a pregnancy exposure registry that monitors pregnancy outcomes in women exposed to ADHD medications, including clonidine hydrochloride extended-release tablets, during pregnancy. Healthcare providers are encouraged to register patients by calling the National Pregnancy Registry for ADHD Medications at 1-866-961-2388 or visiting https://womensmentalhealth.org/adhd-medications/.

Risk Summary

Prolonged experience with clonidine in pregnant women over several decades, based on published literature, including controlled trials, a retrospective cohort study and case reports, have not identified a drug associated risk of major birth defects, miscarriage, and adverse maternal or fetal outcomes. In animal embryofetal studies, increased resorptions were seen in rats and mice administered oral clonidine hydrochloride from implantation through organogenesis at 10 and 5 times, respectively, the maximum recommended human dose (MRHD) given to adolescents on a mg/m^2 basis. No developmental effects were seen in rabbits administered oral clonidine hydrochloride during organogenesis at doses up to 3 times the MRHD (see Data).

The estimated background risk of major birth defects and miscarriage for the indicated population is unknown. All pregnancies have a background risk of birth defect, loss, or other adverse outcomes. In the U.S. general population, the estimated background risk of major birth defects and miscarriages in clinically recognized pregnancies is 2 to 4% and 15 to 20%, respectively.

Data

Animal Data

Oral administration of clonidine hydrochloride to pregnant rabbits during the period of embryo/fetal organogenesis at doses of up to 80 mcg/kg/day (approximately 3 times the oral maximum recommended daily dose [MRHD] of 0.4 mg/day given to adolescents on a mg/m^2 basis) produced no developmental effects. In pregnant rats, however, doses as low as 15 mcg/kg/day (1/3 the MRHD given to adolescents on a mg/m^2 basis) were associated with increased resorptions in a study in which dams were treated continuously from 2 months prior to mating and throughout gestation. Increased resorptions were not associated with treatment at the same or at higher dose levels (up to 3 times the MRHD) when treatment of the dams was restricted to gestation days 6-15. Increases in resorptions were observed in both rats and mice at 500 mcg/kg/day (10 and 5 times the MRHD in rats and mice, respectively) or higher when the animals were treated on gestation days 1-14; 500 mcg/kg/day was the lowest dose employed in this study.

8.2 Lactation

Risk Summary

Based on published lactation studies, clonidine hydrochloride is present in human milk at relative infant doses ranging from 4.1 to 8.4% of the maternal weight-adjusted dosage. Although in most cases, there were no reported adverse effects in breastfed infants exposed to clonidine, there is one case report of sedation, hypotonia, and apnea in an infant exposed to clonidine through breast milk. If an infant is exposed to clonidine hydrochloride through breastmilk, monitor for symptoms of hypotension and bradycardia, such as sedation, lethargy, tachypnea and poor feeding (see Clinical Considerations).The developmental and health benefits of breastfeeding should be considered along with the mother's clinical need for clonidine hydrochloride extended-release tablets and any potential adverse effects on the breastfed child from clonidine hydrochloride extended-release tablets or from the underlying maternal condition. Exercise caution when clonidine hydrochloride extended-release tablets are administered to a nursing woman.

Clinical Considerations

Monitor breastfeeding infants exposed to clonidine hydrochloride extended-release tablets through breast milk for symptoms of hypotension and/or bradycardia such as sedation, lethargy, tachypnea, and poor feeding.

8.3 Females and Males of Reproductive Potential

Infertility

Based on findings in Animal studies revealed that clonidine hydrochloride extended-release tablets may impair fertility in females and males of reproductive potential [see Nonclinical Toxicology (13.1)].

8.4 Pediatric Use

The safety and efficacy of clonidine hydrochloride extended-release tablets in the treatment of ADHD have been established in pediatric patients 6 to 17 years of age. Use of clonidine hydrochloride extended-release tablets in pediatric patients 6 to 17 years of age is supported by three adequate and well-controlled studies; a short-term, placebo-controlled monotherapy trial, a short- term adjunctive therapy trial and a longer-term randomized monotherapy trial [see Clinical Studies (14)]. Safety and efficacy in pediatric patients below the age of 6 years has not been established.

Juvenile Animal Data

In studies in juvenile rats, clonidine hydrochloride alone or in combination with methylphenidate had an effect on bone growth at clinically relevant doses and produced a slight delay in sexual maturation in males at 3 times the maximum recommended human dose (MRHD) for clonidine and methylphenidate.

In a study where juvenile rats were treated orally with clonidine hydrochloride from day 21 of age to adulthood, a slight delay in onset of preputial separation (delayed sexual maturation) was seen in males treated with 300 mcg/kg/day, which is approximately 3 times the MRHD of 0.4 mg/day on a mg/m^2 basis. The no-effect dose was 100 mcg/kg/day, which is approximately equal to the MRHD. There was no drug effects on fertility or on other measures of sexual or neurobehavioral development.

In a study where juvenile rats were treated with clonidine alone (300 mcg/kg/day) or in combination with methylphenidate (10 mg/kg/day in females and 50/30 mg/kg/day in males; the dose was lowered from 50 to 30 mg/kg/day in males due to self-injurious behavior during the first week of treatment) from day 21 of age to adulthood, decreases in bone mineral density and mineral content were observed in males treated with 300 mcg/kg/day clonidine alone and in combination with 50/30 mg/kg/day methylphenidate and a decrease in femur length was observed in males treated with the combination at the end of the treatment period. These doses are approximately 3 times the MRHD of 0.4 mg/day clonidine and 54 mg/day methylphenidate on a mg/m^2 basis. All these effects in male were not reversed at the end of a 4-week recovery period. In addition, similar findings were seen in males treated with a lower dose of clonidine (30 mcg/kg/day) in combination with 50 mg/kg/day of methylphenidate and a decrease in femur length was observed in females treated with clonidine alone at the end of the recovery period. These effects were accompanied by a decrease in body weight gain in treated animals during the treatment period but the effect was reversed at the end of the recovery period. A delay in preputial separation (sexual maturation) was observed in males treated with the combination treatment of 300 mcg/kg/day clonidine and 50/30 mg/kg/day methylphenidate. There was no effect on reproduction or sperm analysis in these males.

8.6 Renal Impairment

The impact of renal impairment on the pharmacokinetics of clonidine in children has not been assessed. The initial dosage of clonidine hydrochloride extended-release tablets should be based on degree of impairment. Monitor patients carefully for hypotension and bradycardia, and titrate to higher doses cautiously. Since only a minimal amount of clonidine is removed during routine hemodialysis, there is no need to give supplemental clonidine hydrochloride extended-release tablets following dialysis.

9 DRUG ABUSE AND DEPENDENCE

9.1 Controlled Substance

Clonidine hydrochloride extended-release tablets is not a controlled substance and has no known potential for abuse or dependence.

10 OVERDOSAGE

Symptoms

Clonidine overdose: hypertension may develop early and may be followed by hypotension, bradycardia, respiratory depression, hypothermia, drowsiness, decreased or absent reflexes, weakness, irritability and miosis. The frequency of CNS depression may be higher in children than adults. Large overdoses may result in reversible cardiac conduction defects or dysrhythmias, apnea, coma and seizures. Signs and symptoms of overdose generally occur within 30 minutes to two hours after exposure.

Treatment

Consult with a Certified Poison Control Center (1-800-222-1222) for up-to-date guidance and advice.

11 DESCRIPTION

Clonidine hydrochloride extended-release is a centrally acting alpha2-adrenergic agonist available as 0.1 mg extended-release tablets for oral administration. Each 0.1 mg tablet is equivalent to 0.087 mg of the free base.

The inactive ingredients are povidone, sodium lauryl sulfate, lactose monohydrate, microcrystalline cellulose, hypromellose, colloidal silicon dioxide and magnesium stearate. The formulation is designed to delay the absorption of active drug in order to decrease peak to trough plasma concentration differences. Clonidine hydrochloride is an imidazoline derivative and exists as a mesomeric compound. The chemical name is 2-(2,6-dichlorophenylamino)-2-imidazoline hydrochloride. The following is the structural formula:

Clonidine hydrochloride is an odorless, bitter, white, crystalline substance soluble in water and alcohol.

12 CLINICAL PHARMACOLOGY

12.1 Mechanism of Action

Clonidine stimulates alpha2-adrenergic receptors in the brain. Clonidine is not a central nervous system stimulant. The mechanism of action of clonidine in ADHD is not known.

12.2 Pharmacodynamics

Clonidine is a known antihypertensive agent. By stimulating alpha2-adrenergic receptors in the brain stem, clonidine reduces sympathetic outflow from the central nervous system and decreases peripheral resistance, renal vascular resistance, heart rate, and blood pressure.

12.3 Pharmacokinetics

Single-dose Pharmacokinetics in Adults

Immediate-release clonidine hydrochloride and clonidine hydrochloride extended-release tablets have different pharmacokinetic characteristics; dose substitution on a milligram for milligram basis will result in differences in exposure. A comparison across studies suggests that the Cmax is 50% lower for clonidine hydrochloride extended-release tablets compared to immediate-release clonidine hydrochloride.

Following oral administration of an immediate release formulation, plasma clonidine concentration peaks in approximately 3 to 5 hours and the plasma half- life ranges from 12 to 16 hours. The half-life increases up to 41 hours in patients with severe impairment of renal function. Following oral administration about 40-60% of the absorbed dose is recovered in the urine as unchanged drug in 24 hours.

About 50% of the absorbed dose is metabolized in the liver. Although studies of the effect of renal impairment and studies of clonidine excretion have not been performed with clonidine hydrochloride extended-release tablets, results are likely to be similar to those of the immediate release formulation.

The pharmacokinetic profile of clonidine hydrochloride extended-release tablets administration was evaluated in an open-label, three-period, randomized, crossover study of 15 healthy adult subjects who received three single-dose regimens of clonidine: 0.1 mg of clonidine hydrochloride extended-release tablets under fasted conditions, 0.1 mg of clonidine hydrochloride extended-release tablets following a high fat meal, and 0.1 mg of clonidine hydrochloride immediate-release tablets under fasted conditions. Treatments were separated by one-week washout periods.

Mean concentration-time data from the 3 treatments are shown in Table 7 and Figure 1. After administration of clonidine hydrochloride extended-release tablets, maximum clonidine concentrations were approximately 50% of the clonidine hydrochloride immediate-release tablets maximum concentrations and occurred approximately 5 hours later relative to clonidine hydrochloride immediate-release tablets. Similar elimination half-lives were observed and total systemic bioavailability following clonidine hydrochloride extended-release tablets was approximately 89% of that following clonidine hydrochloride immediate-release tablets.

Food had no effect on plasma concentrations, bioavailability, or elimination half-life.

Multiple-dose Pharmacokinetics in Children and Adolescents

Plasma clonidine concentrations in children and adolescents (0.1 mg bid and 0.2 mg bid) with ADHD are greater than those of adults with hypertension with children and adolescents receiving higher doses on a mg/kg basis. Body weight normalized clearance (CL/F) in children and adolescents was higher than CL/F observed in adults with hypertension. Clonidine concentrations in plasma increased with increases in dose over the dose range of 0.2 to 0.4 mg/day. Clonidine CL/F was independent of dose administered over the 0.2 to 0.4 mg/day dose range. Clonidine CL/F appeared to decrease slightly with increases in age over the range of 6 to 17 years, and females had a 23% lower CL/F than males. The incidence of "sedation-like" AEs (somnolence and fatigue) appeared to be independent of clonidine dose or concentration within the studied dose range in the titration study. Results from the add-on study showed that clonidine CL/F was 11% higher in patients who were receiving methylphenidate and 44% lower in those receiving amphetamine compared to subjects not on adjunctive therapy.

13 NONCLINICAL TOXICOLOGY

13.1 Carcinogenesis, Mutagenesis and Impairment of Fertility

Carcinogenesis

Clonidine HCl was not carcinogenic when administered in the diet of rats (for up to 132 weeks) or mice (for up to 78 weeks) at doses of up to 1620 (male rats), 2040 (female rats), or 2500 (mice) mcg/kg/day. These doses are approximately 20, 25, and 15 times, respectively, the maximum recommended human dose (MRHD) of 0.4 mg/day on a mg/m^2 basis.

Mutagenesis

There was no evidence of genotoxicity in the Ames test for mutagenicity or mouse micronucleus test for clastogenicity.

Impairment of Fertility

In a reproduction study fertility of female rats appeared to be adversely affected at dose levels of 500 and 2000 mcg/kg/day (10 and 40 times the MRHD on a mg/ m^2 basis). Lower doses have not been adequately evaluated and a no adverse effect level could not be established.

14 CLINICAL STUDIES

Efficacy of clonidine hydrochloride extended-release tablets in the treatment of ADHD was established in children and adolescents (6 to 17 years) in:

• One short-term, placebo-controlled monotherapy trial (Study 1)

• One short-term adjunctive therapy to psychostimulants trial (Study 2)

• One randomized withdrawal trial as monotherapy (Study 3)

Short-term Monotherapy and Adjunctive Therapy to Psychostimulant Studies for ADHD

The efficacy of clonidine hydrochloride extended-release tablets in the treatment of ADHD was established in 2 (one monotherapy and one adjunctive therapy) placebo-controlled trials in pediatric patients aged 6 to 17, who met DSM-IV criteria of ADHD hyperactive or combined hyperactive/inattentive subtypes. Signs and symptoms of ADHD were evaluated using the investigator administered and scored ADHD Rating Scale-IV-Parent Version (ADHDRS-IV) total score including hyperactive/impulsivity and inattentive subscales.

Study 1 (CLON-301), was an 8-week randomized, double-blind, placebo-controlled, fixed dose study of children and adolescents aged 6 to 17 (N=236) with a 5-week primary efficacy endpoint. Patients were randomly assigned to one of the following three treatment groups: clonidine hydrochloride extended-release tablets (CLON) 0.2 mg/day (N=78), clonidine hydrochloride extended-release tablets 0.4 mg/day (N=80), or placebo (N=78). Dosing for the clonidine hydrochloride extended-release tablets groups started at 0.1 mg/day and was titrated in increments of 0.1 mg/week to their respective dose (as divided doses). Patients were maintained at their dose for a minimum of 2 weeks before being gradually tapered down to 0.1 mg/day at the last week of treatment. At both doses, improvements in ADHD symptoms were statistically significantly superior in clonidine hydrochloride extended-release tablets-treated patients compared with placebo-treated patients at the end of 5 weeks as measured by the ADHDRS-IV total score (Table 8).

Study 2 (CLON-302) was an 8-week randomized, double-blind, placebo-controlled, flexible dose study in children and adolescents aged 6 to 17 (N=198) with a 5-week primary efficacy end point. Patients had been treated with a psychostimulant (methylphenidate or amphetamine) for four weeks with inadequate response. Patients were randomly assigned to one of two treatment groups: clonidine hydrochloride extended-release tablets adjunct to a psychostimulant (N=102) or psychostimulant alone (N=96). The clonidine hydrochloride extended-release tablets dose was initiated at 0.1 mg/day and doses were titrated in increments of 0.1 mg/week up to 0.4 mg/day, as divided doses, over a 3-week period based on tolerability and clinical response. The dose was maintained for a minimum of 2 weeks before being gradually tapered to 0.1 mg/day at the last week of treatment. ADHD symptoms were statistically significantly improved in clonidine hydrochloride extended-release tablets plus stimulant group compared with the stimulant alone group at the end of 5 weeks as measured by the ADHDRS-IV total score (Table 8).

Maintenance Monotherapy for ADHD

Study 3 (SHN-KAP-401), was a double-blind, placebo-controlled, randomized-withdrawal study in children and adolescents aged 6 to 17 years (n=253) with DSM-IV-TR diagnosis of ADHD. The study consisted of a 10-week, open-label phase (4 weeks of dose optimization and 6 weeks of dose maintenance), a 26-week double-blind phase, and a 4-week taper-down and follow-up phase. All patients were initiated at 0.1 mg/day and increased at weekly intervals in increments of 0.1 mg/day until reaching personalized optimal dose (0.1, 0.2, 0.3 or 0.4 mg/day, as divided doses). Eligible patients had to demonstrate treatment response as defined by >= 30% reduction in ADHD-RS-IV total score and a Clinical Global Impression-Improvement score of 1 or 2 during the open label phase. Patients who sustained treatment response (n=135) until the end of the open label phase were randomly assigned to one of the two treatment groups, clonidine hydrochloride extended-release tablets (N=68) and Placebo (N=67), to evaluate the long-term efficacy of maintenance dose of clonidine hydrochloride extended-release tablets in the double-blind phase. The primary efficacy endpoint was the percentage of patients with treatment failure defined as a >= 30% increase (worsening) in ADHD-RS-IV total score and >= 2 points increase (worsening) in Clinical Global Impression – Severity Scale in 2 consecutive visits or early termination for any reason. A total of 73 patients experienced treatment failure in the double-blind phase: 31 patients (45.6%) in the clonidine hydrochloride extended-release tablets group and 42 patients (62.7%) in the placebo group, with a statistically significant difference in the primary endpoint favoring clonidine hydrochloride extended-release tablets (Table 9). The cumulative proportion of patients with treatment failure over time during the double-blind phase is displayed in Figure 2.

16 HOW SUPPLIED/STORAGE AND HANDLING

Clonidine hydrochloride extended-release tablets are white or off white, non-scored, round biconvex with debossing ("NL 7") on one side.

NDC 50742-247-30 – 0.1 mg round tablets supplied in bottles containing 30 tablets.

NDC 50742-247-60 – 0.1 mg round tablets supplied in bottles containing 60 tablets.

NDC 50742-247-05 – 0.1 mg round tablets supplied in bottles containing 500 tablets.

Store at 20°-25°C (68°-77°F) [see USP Controlled Room Temperature].

Dispense in a tight container.

17 PATIENT COUNSELING INFORMATION

Advise the patient to read the FDA-approved Patient Labeling (Patient Information)

Dosage and Administration

Advise patients that clonidine hydrochloride extended-release tablets must be swallowed whole, never crushed, cut, or chewed, and may be taken with or without food. When initiating treatment, provide dosage escalation instructions [see Dosage and Administration (2.1)].

Missed Dose

If patients miss a dose of clonidine hydrochloride extended-release tablets, advise them to skip the dose and take the next dose as scheduled and not to take more than the prescribed total daily amount of clonidine hydrochloride extended-release tablets in any 24-hour period [see Dosage and Administration (2.4)].

Hypotension/Bradycardia

Advise patients who have a history of syncope or may have a condition that predisposes them to syncope, such as hypotension, orthostatic hypotension, bradycardia, or dehydration, to avoid becoming dehydrated or overheated [see Warnings and Precautions (5.1)].

Sedation and Somnolence

Instruct patients to use caution when driving a car or operating hazardous machinery until they know how they will respond to treatment with clonidine hydrochloride extended-release tablets. Also advise patients to avoid the use of clonidine hydrochloride extended-release tablets with other centrally active depressants and with alcohol [see Warnings and Precautions (5.2)].

Rebound Hypertension

Advise patients not to discontinue clonidine hydrochloride extended-release tablets abruptly [see Warnings and Precautions (5.3)].

Allergic Reactions

Advise patients to discontinue clonidine hydrochloride extended-release tablets and seek immediate medical attention if any signs or symptoms of a hypersensitivity reaction occur, such as generalized rash, urticaria, or angioedema [see Warnings and Precautions (5.4)].

Pregnancy Registry

Advise patients that there is a pregnancy exposure registry that monitors pregnancy outcomes in patients exposed to clonidine hydrochloride extended-release tablets during pregnancy [see Use in Specific Populations (8.1)].

Lactation

Advise breastfeeding women using clonidine hydrochloride extended-release tablets to monitor infants for excess sedation, decreased muscle tone, and respiratory depression and to seek medical care if they notice these signs [see Use in Specific Populations (8.2)].

Fertility

Advise females and males of reproductive potential that clonidine hydrochloride extended-release tablets may impair fertility [see Use in Specific Populations (8.3) and Nonclinical Toxicology (13.1)].

Rx Only

Manufactured for:

Ingenus Pharmaceuticals, LLC

Orlando, FL 32839-6408

Made in China. Revised: 04/2020

Patient Information

Clonidine Hydrochloride

(KLOE-ni-deen HYE-droe-KLOR-ide)

Extended-Release Tablets

Read the Patient Information that comes with clonidine hydrochloride extended-release tablets before you start taking it and each time you get a refill. There may be new information. This Patient Information leaflet does not take the place of talking to your doctor about your medical condition or treatment.

What are clonidine hydrochloride extended-release tablets?

Clonidine hydrochloride extended-release tablets is a prescription medicine used for the treatment of Attention-Deficit Hyperactivity Disorder (ADHD). Your doctor may prescribe clonidine hydrochloride extended-release tablets alone or together with certain other ADHD medicines.

• Clonidine hydrochloride extended-release tablets is not a central nervous system (CNS) stimulant.

• Clonidine hydrochloride extended-release tablets should be used as part of a total treatment program for ADHD that may include counseling or other therapies.

Who should not take clonidine hydrochloride extended-release tablets?

• Do not take clonidine hydrochloride extended-release tablets if you are allergic to clonidine in clonidine hydrochloride extended-release tablets. See the end of this leaflet for a complete list of ingredients in clonidine hydrochloride extended-release tablets.

What should I tell my doctor before taking clonidine hydrochloride extended-release tablets?

Before you take clonidine hydrochloride extended-release tablets, tell your doctor if you:

• have kidney problems

• have low or high blood pressure

• have a history of passing out (syncope)

• have heart problems, including history of heart attack

• have had a stroke or have stroke symptoms

• had a skin reaction (such as a rash) after taking clonidine in a transdermal form (skin patch)

• have any other medical conditions

• are pregnant or plan to become pregnant. It is not known if clonidine hydrochloride extended-release tablets will harm your unborn baby. Talk to your doctor if you are pregnant or plan to become pregnant.

There is a pregnancy registry for females who are exposed to ADHD medications, including clonidine hydrochloride extended-release tablets, during pregnancy. The purpose of the registry is to collect information about the health of females exposed to clonidine hydrochloride extended-release tablets and their baby. If you or your child becomes pregnant during treatment with clonidine hydrochloride extended-release tablets, talk to your healthcare provider about registering with the National Pregnancy Registry of ADHD Medications at 1-866-961-2388 or visit online at https://womensmentalhealth.org/adhdmedications/.

• are breastfeeding or plan to breastfeed. Clonidine hydrochloride passes into your breast milk. Talk to your doctor about the best way to feed your baby if you take clonidine hydrochloride extended-release tablets.

Tell your doctor about all of the medicines that you take, including prescription and non-prescription medicines, vitamins, and herbal supplements.

Clonidine hydrochloride extended-release tablets and certain other medicines may affect each other causing serious side effects. Sometimes the doses of other medicines may need to be changed while taking clonidine hydrochloride extended-release tablets.

Especially tell your doctor if you take:

• anti-depression medicines

• heart or blood pressure medicine

• other medicines that contain clonidine

• a medicine that makes you sleepy (sedation)

Ask your doctor or pharmacist for a list of these medicines, if you are not sure if your medicine is listed above.

Know the medicines that you take. Keep a list of your medicines with you to show your doctor and pharmacist when you get a new medicine.

How should I take clonidine hydrochloride extended-release tablets?

• Take clonidine hydrochloride extended-release tablets exactly as your doctor tells you to take it.

• Your doctor will tell you how many clonidine hydrochloride extended-release tablets to take and when to take them. Your doctor may change your dose of clonidine hydrochloride extended-release tablets. Do not change your dose of clonidine hydrochloride extended-release tablets without talking to your doctor.

• Do not stop taking clonidine hydrochloride extended-release tablets without talking to your doctor.

• Clonidine hydrochloride extended-release tablets can be taken with or without food.

• Clonidine hydrochloride extended-release tablets should be taken 2 times a day (in the morning and at bedtime).

• If you miss a dose of clonidine hydrochloride extended-release tablets, skip the missed dose. Just take the next dose at your regular time. Do not take two doses at the same time.

• Take clonidine hydrochloride extended-release tablets whole. Do not chew, crush or break clonidine hydrochloride extended-release tablets. Tell your doctor if you cannot swallow clonidine hydrochloride extended-release tablets whole. You may need a different medicine.

• If you take too much clonidine hydrochloride extended-release tablets, call your Poison Control Center or go to the nearest hospital emergency room right away.

What should I avoid while taking clonidine hydrochloride extended-release tablets?

• Do not drink alcohol or take other medicines that make you sleepy or dizzy while taking clonidine hydrochloride extended-release tablets until you talk with your doctor. Clonidine hydrochloride extended-release tablets taken with alcohol or medicines that cause sleepiness or dizziness may make your sleepiness or dizziness worse.

• Do not drive, operate heavy machinery or do other dangerous activities until you know how clonidine hydrochloride extended-release tablets will affect you.

• Avoid becoming dehydrated or overheated.

What are possible side effects of clonidine hydrochloride extended-release tablets?

Clonidine hydrochloride extended-release tablets may cause serious side effects, including:

• Low blood pressure and low heart rate. Your doctor should check your heart rate and blood pressure before starting treatment and regularly during treatment with clonidine hydrochloride extended-release tablets.

• Sleepiness.

• Withdrawal symptoms. Suddenly stopping clonidine hydrochloride extended-release tablets may cause withdrawal symptoms including: increased blood pressure, headache, increased heart rate, lightheadedness, tightness in your chest and nervousness.

The most common side effects of clonidine hydrochloride extended-release tablets include:

• sleepiness

• tiredness

• irritability

• trouble sleeping (insomnia)

• nightmare

• constipation

• dry mouth

• decreased appetite

• dizziness

Tell your doctor if you have any side effects that bother you or that does not go away.

These are not all of the possible side effects of clonidine hydrochloride extended-release tablets. For more information, ask your doctor or pharmacist.

Call your doctor for medical advice about side effects. You may report side effects to FDA at 1-800-FDA-1088.

How should I store clonidine hydrochloride extended-release tablets?

• Store clonidine hydrochloride extended-release tablets between 68°-77°F (20°-25°C).

• Keep clonidine hydrochloride extended-release tablets in a tightly closed container.

Keep clonidine hydrochloride extended-release tablets and all medicines out of the reach of children.

General information about the safe and effective use of clonidine hydrochloride extended-release tablets

Medicines are sometimes prescribed for purposes other than those listed in a Patient Information leaflet. Do not use clonidine hydrochloride extended-release tablets for a condition for which it was not prescribed.

Do not give clonidine hydrochloride extended-release tablets to other people, even if they have the same symptoms that you have. It may harm them.

This Patient Information leaflet summarizes the most important information about clonidine hydrochloride extended-release tablets. If you would like more information, talk with your doctor. You can also ask your doctor or pharmacist for information about clonidine hydrochloride extended-release tablets that is written for healthcare professionals.

What are the ingredients in clonidine hydrochloride extended-release tablets?

• Active Ingredient: clonidine hydrochloride

• Inactive Ingredients: povidone, sodium lauryl sulfate, lactose monohydrate, microcrystalline cellulose, hypromellose, colloidal silicon dioxide and magnesium stearate

Manufactured for:

Ingenus Pharmaceuticals, LLC

Orlando, FL 32839-6408

Made in China.

Revised: 04/2020